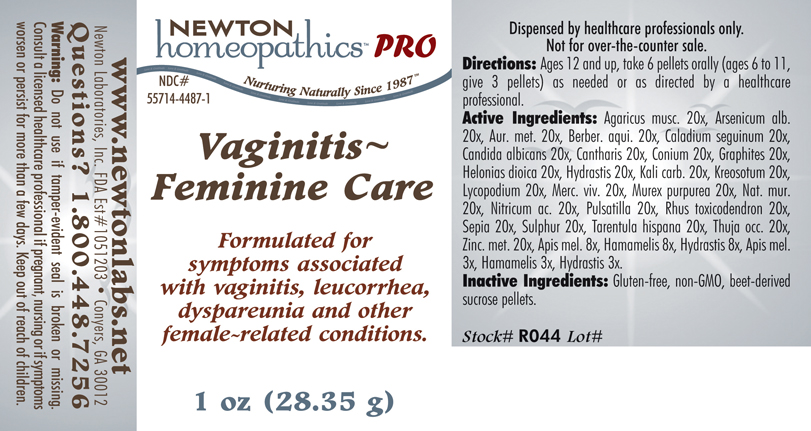 DRUG LABEL: Vaginitis - Feminine Care 
NDC: 55714-4487 | Form: PELLET
Manufacturer: Newton Laboratories, Inc.
Category: homeopathic | Type: HUMAN PRESCRIPTION DRUG LABEL
Date: 20110601

ACTIVE INGREDIENTS: Amanita Muscaria Var. Muscaria Fruiting Body 20 [hp_X]/1 g; Arsenic Trioxide 20 [hp_X]/1 g; Gold 20 [hp_X]/1 g; Mahonia Aquifolium Root Bark 20 [hp_X]/1 g; Dieffenbachia Seguine 20 [hp_X]/1 g; Candida Albicans 20 [hp_X]/1 g; Lytta Vesicatoria 20 [hp_X]/1 g; Conium Maculatum Flowering Top 20 [hp_X]/1 g; Graphite 20 [hp_X]/1 g; Chamaelirium Luteum Root 20 [hp_X]/1 g; Goldenseal 20 [hp_X]/1 g; Potassium Carbonate 20 [hp_X]/1 g; Wood Creosote 20 [hp_X]/1 g; Lycopodium Clavatum Spore 20 [hp_X]/1 g; Mercury 20 [hp_X]/1 g; Sodium Chloride 20 [hp_X]/1 g; Nitric Acid 20 [hp_X]/1 g; Pulsatilla Vulgaris 20 [hp_X]/1 g; Toxicodendron Pubescens Leaf 20 [hp_X]/1 g; Sepia Officinalis Juice 20 [hp_X]/1 g; Sulfur 20 [hp_X]/1 g; Lycosa Tarantula 20 [hp_X]/1 g; Thuja Occidentalis Leafy Twig 20 [hp_X]/1 g; Zinc 20 [hp_X]/1 g; Apis Mellifera 8 [hp_X]/1 g; Hamamelis Virginiana Root Bark/stem Bark 8 [hp_X]/1 g; Hexaplex Trunculus Hypobranchial Gland Juice 20 [hp_X]/1 g
INACTIVE INGREDIENTS: Sucrose

Vaginitis - Feminine Care

INDICATIONS & USAGE SECTION

Vaginitis - Feminine Care Formulated for symptoms associated with vaginitis and leucorrhea such as itching, burning, dryness, swelling, snoreness and discharge.

DOSAGE & ADMINISTRATION SECTION

Directions: Ages 12 and up, take 6 pellets orally (ages 6 to 11, give 3 pellets) as needed or as directed by a healthcare professional.

ACTIVE INGREDIENT SECTION

Agaricus musc. 20x, Arsenicum alb. 20x, Aur. met. 20x, Berber. aqui. 20x, Caladium seguinum 20x, Candida albicans 20x, Cantharis 20x, Conium 20x, Graphites 20x, Helonias dioica 20x, Hydrastis 20x, Kali carb. 20x, Kreosotum 20x, Lycopodium 20x, Merc. viv. 20x, Murex purpurea 20x, Nat. mur. 20x, Nitricum ac. 20x, Pulsatilla 20x, Rhus toxicodendron 20x, Sepia 20x, Sulphur 20x, Tarentula hispana 20x, Thuja occ. 20x, Zinc. met. 20x, Apis mel. 8x, Hamamelis 8x, Hydrastis 8x, Apis mel. 3x, Hamamelis 3x, Hydrastis 3x.

PURPOSE SECTION

Formulated for symptoms associated with vaginitis and leucorrhea such as itching, burning, dryness, swelling, snoreness and discharge.

INACTIVE INGREDIENT SECTION

Inactive Ingredients: Gluten-free, non-GMO, beet-derived sucrose pellets.

QUESTIONS? SECTION

www.newtonlabs.net Newton Laboratories, Inc. FDA Est # 1051203 - Conyers, GA 30012
Questions? 1.800.448.7256

WARNINGS SECTION

Warning: Do not use if tamper - evident seal is broken or missing. Consult a licensed healthcare professional if pregnant, nursing or if symptoms worsen or persist for more than a few days. Keep out of reach of children.

PREGNANCY OR BREAST FEEDING SECTION

Consult a licensed healthcare professional if pregnant, nursing or if symptoms worsen or persist for more than a few days.

KEEP OUT OF REACH OF CHILDREN SECTION

Keep out of reach of children.